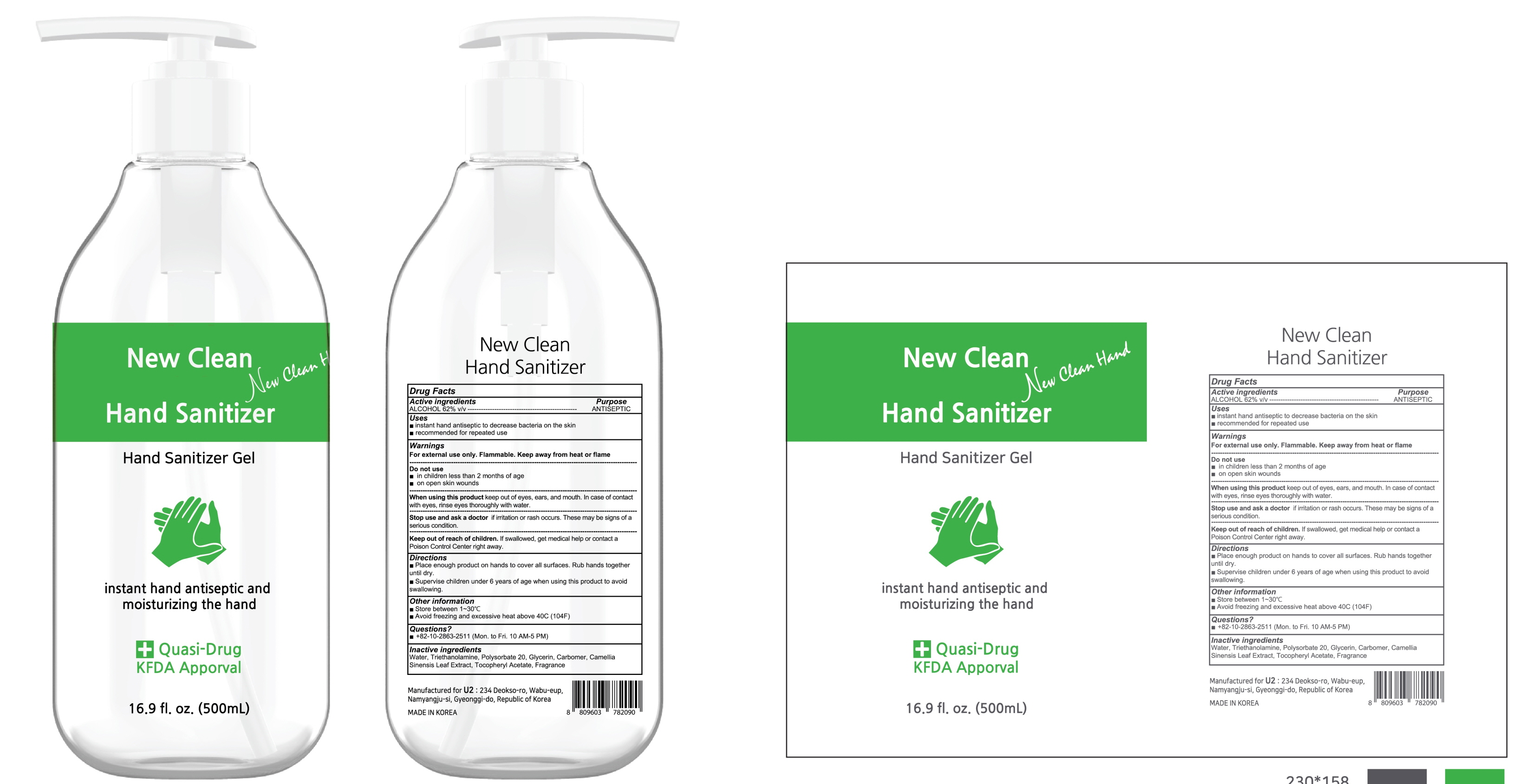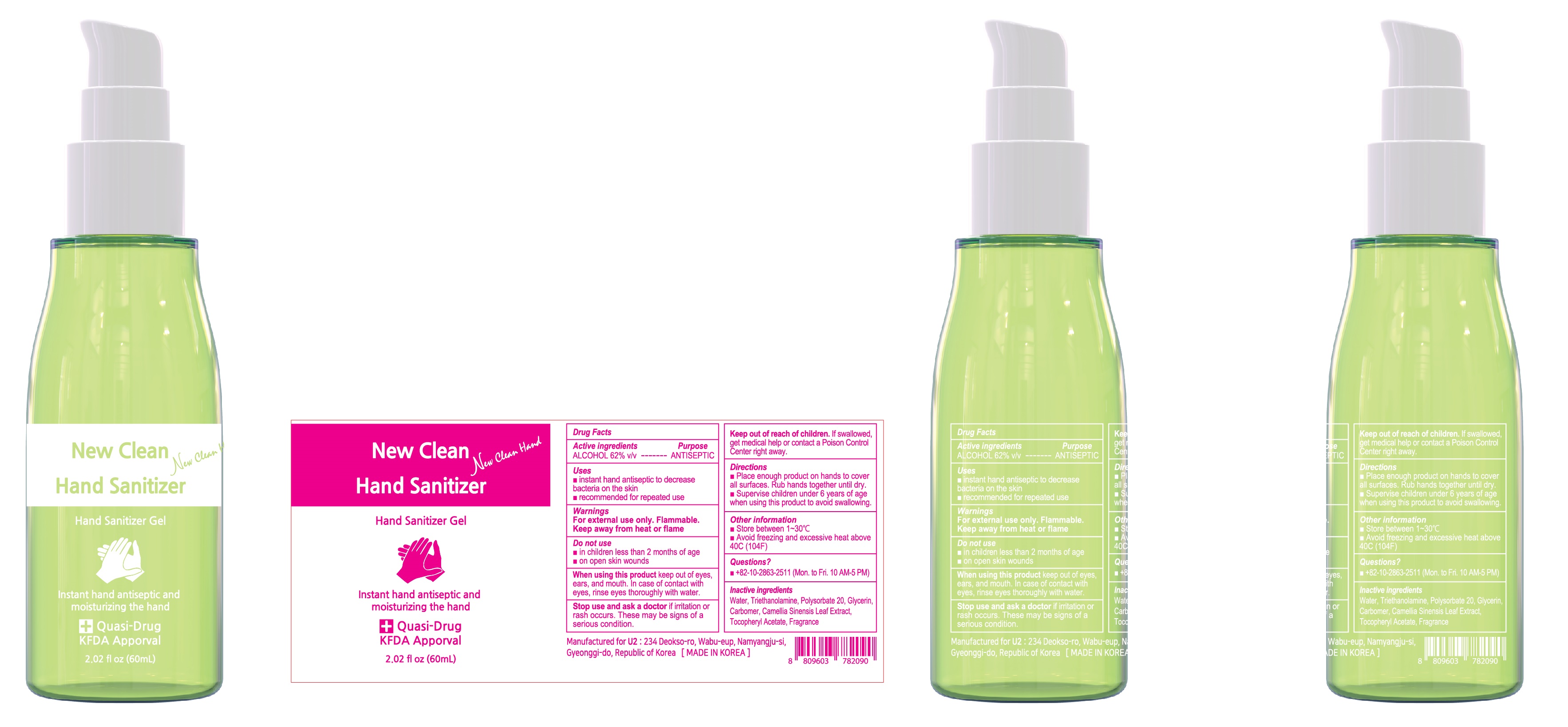 DRUG LABEL: New Clean Hand Sanitizer
NDC: 78023-010 | Form: GEL
Manufacturer: U2
Category: otc | Type: HUMAN OTC DRUG LABEL
Date: 20200520

ACTIVE INGREDIENTS: ALCOHOL 62 mL/100 mL
INACTIVE INGREDIENTS: Water; TROLAMINE; Polysorbate 20; Glycerin; CARBOMER HOMOPOLYMER, UNSPECIFIED TYPE; GREEN TEA LEAF; .ALPHA.-TOCOPHEROL ACETATE

ACTIVE INGREDIENT

ALCOHOL 62% v/v

INACTIVE INGREDIENT

Water, Triethanolamine, Polysorbate 20, Glycerin, Carbomer, Camellia Sinensis Leaf Extract, Tocopheryl Acetate, Fragrance

PURPOSE

Antiseptic

WARNINGS

For external use only. Flammable. Keep away from heat or flame
--------------------------------------------------------------------------------------------------------
Do not use
• in children less than 2 months of age
• on open skin wounds
--------------------------------------------------------------------------------------------------------
When using this product keep out of eyes, ears, and mouth. In case of contact with eyes, rinse eyes thoroughly with water.
--------------------------------------------------------------------------------------------------------
Stop use and ask a doctor if irritation or rash occurs. These may be signs of a serious condition.

KEEP OUT OF REACH OF CHILDREN

If swallowed, get medical help or contact a Poison Control Center right away.

Uses

■ instant hand antiseptic to decrease bacteria on the skin
■ recommended for repeated use

Directions

■ Place enough product on hands to cover all surfaces. Rub hands together until dry.
■ Supervise children under 6 years of age when using this product to avoid swallowing.

Other Information

■ Store between 1~30℃
■ Avoid freezing and excessive heat above 40℃ (104F)

Questions?

■ +82-10-2863-2511 (Mon. to Fri. 10 AM-5 PM)